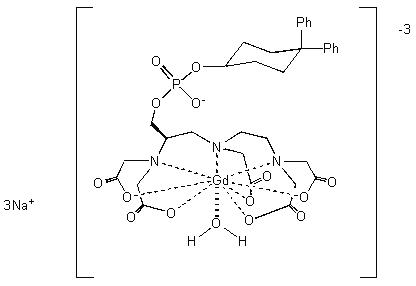 DRUG LABEL: Unknown
Manufacturer: Bayer Healthcare, Inc.
Category: prescription | Type: HUMAN PRESCRIPTION DRUG LABEL WITH HIGHLIGHTS
Date: 20090102

HIGHLIGHTS OF PRESCRIBING INFORMATION

WARNING: NEPHROGENIC SYSTEMIC FIBROSIS (NSF)

See full prescribing information for complete boxed warning

Gadolinium-based contrast agents increase the risk of nephrogenic systemic fibrosis (NSF) in patients with:

- acute or chronic severe renal insufficiency (glomerular filtration rate <30 mL/min/1.73m^2), or
- acute renal insufficiency of any severity due to the hepato-renal syndrome or in the perioperative liver transplantation period.

In these patients, avoid use of gadolinium-based contrast agents unless the diagnostic information is essential and not available with non-contrast enhanced magnetic resonance imaging (MRI). NSF may result in fatal or debilitating systemic fibrosis affecting the skin, muscle, and internal organs. Screen all patients for renal dysfunction by obtaining a history and/or laboratory tests. When administering a gadolinium-based contrast agent, do not exceed the recommended dose and allow a sufficient period of time for elimination of the agent from the body prior to any re-administration [see Warnings and Precautions (5.1)]

1 INDICATIONS AND USAGE

VASOVIST Injection is a gadolinium-based contrast agent indicated for use as a contrast agent in magnetic resonance angiography (MRA) to evaluate aortoiliac occlusive disease (AIOD) in adults with known or suspected peripheral vascular disease .

2 DOSAGE AND ADMINISTRATION

Administer VASOVIST Injection by an intravenous bolus, manually or by power injection, at a dose of 0.12 mL/kg body weight (0.03 mmol/kg) over a period of time up to 30 seconds followed by a 25-30 mL normal saline flush.

Imaging is performed in two stages, the dynamic stage which begins immediately following VASOVIST Injection and the steady-state stage, which begins following dynamic imaging; generally 5 to 7 minutes after VASOVIST Injection.

3 DOSAGE FORMS AND STRENGTHS

Each mL of VASOVIST Injection contains 244 mg gadofosveset trisodium (equivalent to 0.25 mmol/mL) and is available in single-use vials (3).

4 CONTRAINDICATIONS

- History of a prior allergic reaction to a gadolinium-based contrast agent (4).

5 WARNINGS AND PRECAUTIONS

- Nephrogenic Systemic Fibrosis may result from administration of gadolinium-based contrast agents to certain patients (5.1).
- Hypersensitivity reactions, including anaphylactoid and/or anaphylactic reactions may result from VASOVIST administration. Assess patients for a history of allergic reactions to gadolinium-based contrast agents and monitor patients closely for need of emergency cardiorespiratory support (5.2)
- Gadolinium-based contrast agents, including VASOVIST may increase the risk for acute renal failure in patients with a history of renal insufficiency (5.3).
- QTc prolongation has been reported following VASOVIST administration. Assess patients for a history of underlying conditions that may predispose to arrhythmias due to QTc prolongation (5.4).

6 ADVERSE REACTIONS

The most common (>2%) adverse reactions are pruritis, headache, nausea, vasodilatation, and paresthesia (6.1, 6.2)

FULL PRESCRIBING INFORMATION

WARNING: NEPHROGENIC SYSTEMIC FIBROSIS (NSF)

Gadolinium-based contrast agents increase the risk for nephrogenic systemic fibrosis (NSF) in patients with:

- acute or chronic severe renal insufficiency (glomerular filtration rate <30 mL/min/1.73m^2), or
- acute renal insufficiency of any severity due to the hepato-renal syndrome or in the perioperative liver transplantation period.

In these patients, avoid use of gadolinium-based contrast agents unless the diagnostic information is essential and not available with non-contrast enhanced magnetic resonance imaging (MRI). NSF may result in fatal or debilitating systemic fibrosis affecting the skin, muscle, and internal organs. Screen all patients for renal dysfunction by obtaining a history and/or laboratory tests. When administering a gadolinium-based contrast agent, do not exceed the recommended dose and allow a sufficient period of time for elimination of the agent from the body prior to any re-administration [see Warnings and Precautions (5.1)]

1 INDICATIONS AND USAGE

VASOVIST is indicated for use as a contrast agent in magnetic resonance angiography (MRA) to evaluate aortoiliac occlusive disease (AIOD) in adults with known or suspected peripheral vascular disease [see Clinical Studies (14)].

2 DOSAGE AND ADMINISTRATION

2.1 Dosing Guidelines

Administer VASOVIST as an intravenous bolus injection, manually or by power injection, at a dose of 0.12 mL/kg body weight (0.03 mmol/kg) over a period of time up to 30 seconds followed by a 25-30 mL normal saline flush. (See Table 1 for weight-adjusted dose volumes).

TABLE 1. Weight-Adjusted Volumes for the 0.03 mmol/kg Dose
Body Weight |  | Volume
Kilograms (kg) | Pounds (lb) | Milliliters (mL)
40 | 88 | 4.8
50 | 110 | 6.0
60 | 132 | 7.2
70 | 154 | 8.4
80 | 176 | 9.6
90 | 198 | 10.8
100 | 220 | 12.0
110 | 242 | 13.2
120 | 264 | 14.4
130 | 286 | 15.6
140 | 308 | 16.8
150 | 330 | 18.0
160 | 352 | 19.2

Inspect the VASOVIST vial visually for particulate matter and discoloration prior to administration. Do not use the solution if it is discolored or particulate matter is present.

VASOVIST is intended for single use only and should be used immediately upon opening. Discard any unused portion of the VASOVIST vial.

Do not mix intravenous medications or parenteral nutrition solutions with VASOVIST. Do not administer any other medications in the same intravenous line simultaneously with VASOVIST.

2.2 Imaging Guidelines

VASOVIST imaging is completed in two stages: the dynamic imaging stage and the steady-state imaging stage. Both stages are essential for adequate evaluation of the arterial system, and dynamic imaging always precedes steady-state imaging. During interpretation of the steady-state images, VASOVIST within the venous system may limit or confound the detection of arterial lesions.

To assess the initial distribution of VASOVIST within the arterial system, begin dynamic imaging immediately upon injection. Begin steady state imaging after dynamic imaging has been completed, generally 5 to 7 minutes following VASOVIST administration. At this time point, VASOVIST is generally distributed throughout the blood. In clinical trials, steady-state imaging was completed within approximately one hour following VASOVIST injection.

3 DOSAGE FORMS AND STRENGTHS

VASOVIST is a sterile solution for intravenous injection containing 244 mg/mL (0.25 mmol/mL) gadofosveset trisodium [see How Supplied/Storage and Handling (16)]

4 CONTRAINDICATIONS

History of a prior allergic reaction to a gadolinium-based contrast agent.

5 WARNINGS AND PRECAUTIONS

5.1 Nephrogenic Systemic Fibrosis

Gadolinium-based contrast agents increase the risk for nephrogenic systemic fibrosis (NSF) in patients with acute or chronic severe renal insufficiency (glomerular filtration rate <30 mL/min/1.73m^2) and in patients with acute renal insufficiency of any severity due to the hepato-renal syndrome or in the perioperative liver transplantation period. In these patients, avoid use of gadolinium-based contrast agents unless the diagnostic information is essential and not available with non-contrast enhanced MRA. For patients receiving hemodialysis, physicians may consider the prompt initiation of hemodialysis following the administration of a gadolinium-based contrast agent in order to enhance the contrast agent's elimination. VASOVIST binds to blood albumin and use of a high-flux dialysis procedure is essential to optimized VASOVIST elimination in patients receiving chronic hemodialysis. The usefulness of hemodialysis in the prevention of NSF is unknown [see Boxed Warning and Clinical Pharmacology (12.3)].

Among the factors that may increase the risk for NSF are repeated or higher than recommended doses of a gadolinium-based contrast agent and the degree of renal function impairment at the time of exposure.

Post-marketing reports have identified the development of NSF following single and multiple administrations of gadolinium-based contrast agents. These reports have not always identified a specific agent. Prior to marketing of Vasovist®, where a specific agent was identified, the most commonly reported agent was gadodiamide (OmniscanTM), followed by gadopentetate dimeglumine (Magnevist®) and gadoversetamide (OptiMARK®). NSF has also developed following sequential administrations of gadodiamide with gadobenate dimeglumine (MultiHance®) or gadoteridol (ProHance®). The number of post-marketing reports is subject to change over time and may not reflect the true proportion of cases associated with any specific gadolinium-based contrast agent.

The extent of risk for NSF following exposure to any specific gadolinium-based contrast agent is unknown and may vary among the agents. Published reports are limited and predominantly estimate NSF risks with gadodiamide. In one retrospective study of 370 patients with severe renal insufficiency who received gadodiamide, the estimated risk for development of NSF was 4% (J Am Soc Nephrol 2006; 17:2359). The risk, if any, for the development of NSF among patients with mild to moderate renal insufficiency or normal renal function is unknown.

Screen all patients for renal dysfunction by obtaining a history and/or laboratory tests. When administering a gadolinium-based contrast agent, do not exceed the recommended dose and allow a sufficient period of time for elimination of the agent prior to any re-administration. NSF was not reported in clinical trials of VASOVIST [see Clinical Pharmacology (12) and Dosage and Administration (2)].

5.2 Hypersensitivity Reactions

VASOVIST may cause anaphylactoid and/or anaphylactic reactions, including life-threatening or fatal reactions. In clinical trials, anaphylactoid and/or anaphylactic reactions occurred in two of 1676 subjects. If anaphylactic or anaphylactoid reactions occur, stop VASOVIST Injection and immediately begin appropriate therapy. Observe patients closely, particularly those with a history of drug reactions, asthma, allergy or other hypersensitivity disorders, during and up to several hours after VASOVIST administration. Have emergency resuscitative equipment available prior to and during VASOVIST administration.

5.3 Acute Renal Failure

In patients with renal insufficiency, acute renal failure requiring dialysis or worsening renal function have occurred with the use of other gadolinium agents. The risk of renal failure may increase with increasing dose of gadolinium contrast. Screen all patients for renal dysfunction by obtaining a history and/or laboratory tests. Consider follow-up renal function assessments for patients with a history of renal dysfunction. No reports of acute renal failure were observed in clinical trials of VASOVIST [see Clinical Pharmacology (12.3)].

5.4 QTc Prolongation and Risk for Arrhythmias

In clinical trials, a small increase (2.8 msec) in the average change from baseline in QTc was observed at 45 minutes following VASOVIST administration; no increase was observed at 24 and 72 hours. A QTc change of 30 to 60 msec from baseline was observed in 39/702 (6%) patients at 45 min following VASOVIST administration. At this time point, 3/702 (0.4%) patients experienced a QTc increase of > 60 msec. These QTc prolongations were not associated with arrhythmias or symptoms. In patients at high risk for arrhythmias due to QTc prolongation (e.g., concomitant medications, underlying cardiac conditions) consider obtaining baseline electrocardiograms to help assess the risks for VASOVIST administration. If VASOVIST is administered to these patients, consider follow-up electrocardiograms and risk reduction measures (e.g., patient counseling or intensive electrocardiography monitoring) until most VASOVIST has been eliminated from the blood. In patients with normal renal function, most VASOVIST was eliminated from the blood by 72 hours following injection [see Clinical Pharmacology (12.3)].

6 ADVERSE REACTIONS

Because clinical studies are conducted under widely varying conditions, adverse reaction rates observed in the clinical studies of a drug cannot be directly compared to rates in the clinical studies of another drug and may not reflect the rates observed in practice.

6.1 Clinical Studies Experience

Anaphylaxis and anaphylactoid reactions were the most common serious reactions observed following VASOVIST injection administration [see Warnings and Precautions (5.2)].

In all clinical trials evaluating VASOVIST with MRA, a total of 1,676 (1379 patients and 297 healthy subjects) were exposed to various doses VASOVIST. The mean age of the 1379 patients who received VASOVIST was 63 years (range 18 to 91 years); 66% (903) were men and 34% (476) were women. In this population, there were 80% (1100) Caucasian, 8% (107) Black, 12% (159) Hispanic, 1% (7) Asian, and < 1% (6) patients of other racial or ethnic groups. Table 2 shows the most common adverse reactions (≥1%) experienced by subjects receiving VASOVIST at a dose of 0.03 mmol/kg.

Table 2 Common Adverse Reactions in 802 Subjects Receiving VASOVIST at 0.03 mmol/kg
Preferred Term | n (%)
Pruritis | 42 (5)
Headache | 33 (4)
Nausea | 33 (4)
Vasodilatation | 26 (3)
Paresthesia | 25 (3)
Injection site bruising | 19 (2)
Dysgeusia | 18 (2)
Burning sensation | 17 (2)
Venipuncture site bruise | 17 (2)
Hypertension | 11 (1)
Dizziness (excluding vertigo) | 8 (1)
Feeling cold | 7 (1)

6.2 Post-marketing Experience

Because post-marketing reactions are reported voluntarily from a population of uncertain size, it is not always possible to reliably estimate their frequency or establish a causal relationship to drug exposure. The profile of adverse reactions identified during the post-marketing experience outside the United States was similar to that observed during the clinical studies experience.

7 DRUG INTERACTIONS

Following injection, VASOVIST binds to blood albumin and has the potential to alter the binding of other drugs that also bind to albumin. No drug interaction reactions were observed in clinical trials. Consider the possibility of VASOVIST interaction with concomitantly administered medications that bind to albumin. An interaction may enhance or decrease the activity of the concomitant medication [see Clinical Pharmacology (12.3)].

7.1 Warfarin

In a clinical trial of 10 patients receiving a stable dose of warfarin, a single dose of VASOVIST (0.05 mmol/kg) did not alter the anticoagulant activity of warfarin as measured by the International Normalized Ratio (INR).

8 USE IN SPECIFIC POPULATIONS

8.1 Pregnancy

TERATOGENIC EFFECTS

Pregnancy Category C

There are no adequate and well-controlled studies of VASOVIST in pregnant women. In animal studies, pregnant rabbits treated with gadofosveset trisodium at doses 3 times the human dose (based on body surface area) experienced higher rates of fetal loss and resorptions. Because animal reproduction studies are not always predictive of human response, only use VASOVIST during pregnancy if the diagnostic benefit justifies the potential risks to the fetus.

In reproductive studies, pregnant rats and rabbits received gadofosveset trisodium at various doses up to approximately 11 (rats) and 21.5 (rabbits) times the human dose (based on body surface area). The highest dose resulted in maternal toxicity in both species. In rabbits that received gadofosveset trisodium at 3 times the human dose (based on body surface area), increased post-implantation loss, resorptions, and dead fetuses were observed. Fetal anomalies were not observed in the rat or rabbit offspring. Because pregnant animals received repeated daily doses of VASOVIST, their overall exposure was significantly higher than that achieved with a single dose administered to humans.

8.3 Nursing Mothers

It is not known whether gadofosveset is secreted in human milk. Because many drugs are excreted in human milk, caution should be exercised when VASOVIST is administered to a woman who is breastfeeding. The risks associated with exposure of infants to gadolinium-based contrast agents in breast milk are unknown. Limited case reports indicate that 0.01 to 0.04% of the maternal gadolinium dose is excreted in human breast milk. Studies of other gadolinium products have shown limited gastrointestinal absorption. These studies were conducted with gadolinium products with shorter half-lives than VASOVIST. Avoid VASOVIST administration to women who are breastfeeding unless the diagnostic information is essential and not obtainable with non-contrast MRA.

Less than 1% of gadofosveset at doses up to 0.3 mmol/kg was secreted in the milk of lactating rats.

8.4 Pediatric Use

The safety and effectiveness of VASOVIST in patients under 18 years of age have not been established. The risks associated with VASOVIST administration to pediatric patients are unknown and insufficient data are available to establish a dose. Because VASOVIST is eliminated predominantly by the kidneys, pediatric patients with immature renal function may be at particular risk for adverse reactions.

8.5 Geriatric Use

In clinical trials, no overall differences in safety and efficacy were observed between subjects 65 years and older and younger subjects. Whereas current clinical experience has not identified differences in responses between elderly and younger patients, greater susceptibility to adverse experiences of some older individuals cannot be ruled out.

10 OVERDOSAGE

VASOVIST Injection has been administered to humans up to a dose of 0.15 mmol/kg (5 times the clinical dose). No VASOVIST overdoses were reported in clinical trials. In the event of an overdose, direct treatment toward the support of all vital functions and prompt institution of symptomatic therapy. Gadofosveset has been shown to be removed by hemodialysis using a high flux dialysis procedure [see Clinical Pharmacology (12.3)].

11 DESCRIPTION

VASOVIST (gadofosveset trisodium) Injection is a sterile, nonpyrogenic, formulation of a stable gadolinium diethylenetriaminepentaacetic acid (GdDTPA) chelate derivative with a diphenylcyclohexylphosphate group. Each mL of VASOVIST Injection contains 244 mg of gadofosveset trisodium (0.25 mmol), 0.27 mg of fosveset, and water for injection.

It contains no preservative and the solution pH ranges between 6.5 to 8.0.

Gadofosveset trisodium is chemically trisodium-{(2-(R)-[(4,4-diphenylcyclohexyl) phosphonooxymethyl]-diethylenetriaminepentaacetato)(aquo) gadolinium(III),with a molecular weight of 975.88 g/mol, and an empirical formula of C33H40GdN3Na3O15P. It has a structural formula:

Pertinent physiochemical data of VASOVIST Injection are provided below:

Table 3. Physiochemical Characteristics
Parameter | Condition | Value
Osmolality (mOsmol/kg water) | @ 37°C | 825
Viscosity (cP) | @ 20°C | 3.0
Density (g/mL) | @ 25°C | 1.1224

12 CLINICAL PHARMACOLOGY

12.1 Mechanism of Action

Following intravenous injection, gadofosveset binds reversibly to endogenous serum albumin resulting in longer vascular residence time than non-protein binding contrast agents. The binding to serum albumin also increases the magnetic resonance relaxivity of gadofosveset and decreases the relaxation time (T1) of water protons resulting in an increase in signal intensity (brightness) of blood.

12.2 Pharmacodynamics

In human studies, gadofosveset substantially shortened blood T1 values for up to 4 hours after intravenous bolus injection. Relaxivity in plasma was measured to be 33.4 to 45.7 mM^-1s^-1 (0.47 T) over the dose range of up to 0.05 mmol/kg.

12.3 Pharmacokinetics

The pharmacokinetics of intravenously administered gadofosveset conforms to a two-compartment open model with mean plasma concentrations (reported as mean ±SD) of 0.43 ± 0.04 mmol/L at 3 minutes post-injection, and 0.24 ± 0.03 mmol/L at one hour post-injection. The mean half-life of the distribution phase is 0.48 ± 0.11 hours and the mean half-life of the elimination phase is 16.3 ± 2.6 hours. The mean total clearance of gadofosveset is 6.57 ± 0.97 mL/h/kg following the administration of 0.03 mmol/kg.

Distribution: The mean volume of distribution at steady state for gadofosveset was 148 ± 16 mL/kg, roughly equivalent to that of extracellular fluid. A significant portion of circulating gadofosveset is bound to plasma proteins. At 0.05, 0.5, 1 and 4 hours after injection of 0.03 mmol/kg the plasma protein binding of gadofosveset ranges from 79.8 to 87.4%.

Metabolism: Gadofosveset does not undergo measurable metabolism in humans.

Excretion: Gadofosveset is eliminated primarily in the urine with approximately 83.5% of an injected dose excreted in the urine over 14 days. Ninety-four percent (94%) of urinary excretion occurs in the first 72 hours. A small portion of gadofosveset dose is recovered in feces (approximately 4.7%).

Special Populations

Renal Insufficiency: Administration of gadolinium-based contrast agents, including VASOVIST to patients with severe renal insufficiency increases the risk for NSF. Administration of these agents to patients with mild to moderate renal insufficiency may increase the risk for worsened renal function [see Warnings and Precautions (5.1 and 5.3)]. Prior to use of VASOVIST in these patients, ensure that no satisfactory diagnostic alternatives are available. In patients with moderate to severe renal impairment (glomerular filtration rate < 60 mL/kg/m2), administer VASOVIST at a dose of 0.01 mmol/kg to 0.02 mmol/kg. Consider follow-up renal function assessments following VASOVIST administration to any patients with renal insufficiency.

A clinical study of gadofosveset, at a dose of 0.05 mmol/kg, was conducted in patients with mild, moderate, and severe renal impairment. The clearance decreased substantially as renal function decreased and the systemic exposure (AUC) increased almost 1.75-fold in patients with moderate (creatinine clearance: 30 to 50 mL/min) and 2.25-fold in patients with severe renal impairment (creatinine clearance < 30 mL/min). The elimination half-life increased from 19 hours in normal subjects to 49 hours in patients with moderate and 70 hours in patients with severe renal impairment. The volume of distribution at steady state and plasma protein binding of gadofosveset were not affected by renal impairment. Fecal elimination of gadofosveset increased as a function of increasing renal impairment (6.5% in normal subjects to 13.3% in patients with severe renal impairment).

Hemodialysis: Gadofosveset is removed from the body by hemodialysis using high-flux filters. Elimination of the total administered dose of gadolinium in dialysate over 3 dialysis sessions using high-flux filters averaged 46.8%, 12.9%, and 6.11% for the first, second, and third sessions, respectively.

Hepatic Insufficiency: The pharmacokinetics and plasma protein binding of gadofosveset was not significantly influenced by moderate hepatic impairment. A slight decrease in fecal elimination of gadofosveset was seen for the hepatic impaired subjects (2.7%) compared to normal subjects (4.8%).

Gender: No dosage adjustment is necessary based on gender. Gender had no meaningful effect on the pharmacokinetics of gadofosveset.

Geriatric: No dosage adjustment is necessary based on age. Age had no meaningful effect on the pharmacokinetics of gadofosveset.

Pediatric: Studies of gadofosveset in pediatric patients have not been performed.

13 NONCLINICAL TOXICOLOGY

13.1 Carcinogenesis, Mutagenesis, Impairment of Fertility

Long-term animal studies have not been performed to evaluate the carcinogenic potential of gadofosveset. Gadofosveset was negative in the in vitro bacterial reverse mutation assay, in vitro CHO chromosome aberration assay, and the in vivo mouse micronucleus assay. Administration of up to 1.5 mmol/kg (8.3 times the human dose) to female rats for 2 weeks and to male rats for 4 weeks did not impair fertility [see Use in Specific Populations (8.1)].

14 CLINICAL STUDIES

Safety and efficacy of VASOVIST were assessed in two multi-center, open-label, Phase 3 clinical trials. In both trials, patients with known or suspected peripheral vascular disease underwent MRA with and without VASOVIST as well as catheter-based X-ray arteriography. Diagnostic efficacy was based upon comparisons of sensitivity and specificity between MRA with and without VASOVIST, with X-ray arteriography as the reference standard.

Out of 493 patients enrolled in these two trials, 424 were included in the comparison of the diagnostic efficacy of VASOVIST-MRA to that of non-contrast MRA in detection/exclusion of occlusive vascular disease (≥ 50% stenosis) in 7 vessel-segments in the aortoiliac region. The interpretation of MRA images from both trials was conducted by three independent radiologist readers who were blinded to clinical data, including the results of X-ray arteriography. In these 424 patients, the median age was 67 years with a range of 29 to 87 years; 58% of the patients were over 65 years of age; 83% were white and 68% were male.

The primary efficacy analyses were designed to demonstrate superiority in sensitivity and non-inferiority in specificity of VASOVIST-MRA as compared to non-contrast MRA at the vessel-segment level. The uninterpretable images were assigned an outcome of "wrong diagnosis". Additionally, success was also based upon acceptable performance characteristics for the uninterpretable non-contrast MRA vessel segments that became interpretable following VASOVIST administration. Specifically, the sensitivity and specificity for these VASOVIST images were required to exceed 50%. These pre-specified success criteria were to be achieved by at least the same two readers for all primary analyses.

Superiority in sensitivity and non-inferiority in specificity was demonstrated for VASOVIST-MRA by all three blinded readers. On average, 316 vessel segments were assessed for sensitivity and 2230 for specificity, by each reader. Table 4 summarizes the efficacy results, by reader.

Table 4. Performance Characteristics of VASOVIST-MRA and Non-contrast MRA
Reader | SENSITIVITY |  |  | SPECIFICITY
Reader | VASOVIST-MRA [A] | Non-contrast MRA [B] | [A] – [B] (95% CI) [(Based on cluster-corrected McNemar Test)] | VASOVIST MRA [A] | Non-contrast MRA [B] | [A] – [B] (95% CI)
1 | 89% | 69% | 20% (15%, 25%) | 72% | 71% | 1% (-3%, 5%)
2 | 82% | 70% | 12% (7%, 17%) | 81% | 73% | 8% (4%, 12%)
3 | 79% | 64% | 15% (9%, 21%) | 85% | 85% | 0% (-2%, 2%)

Among the three readers, 5 to 12% of the vessel-segments were deemed uninterpretable by non-contrast MRA. For these vessel segments, sensitivity of VASOVIST-MRA ranged from 72% [95% CI (54%, 90%)] to 97% [95% CI (93%, 100%)] and specificity ranged from 72% [95% CI (67%,76%)] to 84% [95% CI (81%, 88%)].

16 HOW SUPPLIED/STORAGE AND HANDLING

VASOVIST Injection is a sterile, clear, colorless to pale yellow solution containing 244 mg/mL (0.25 mmol/mL) of gadofosveset trisodium in rubber-stoppered vials with an aluminum seal. VASOVIST Injection is supplied as follows:

NDC 50419-310-01 - 10 mL fills in 10 mL single use vials packages of 10 vials
NDC 50419-310-02 - 15 mL fills in 20 mL single use vials in packages of 10 vials

STORAGE AND HANDLING

Store VASOVIST Injection at 25°C (77°F: excursions permitted to 15 to 30°C [59 to 86°F]). Protect from light and freezing.

17 PATIENT COUNSELING INFORMATION

Instruct patients receiving VASOVIST Injection to inform their physician or healthcare provider if they:

- are pregnant or breast feeding
- have a history of allergic reaction to contrast media, a history of bronchial asthma or allergic respiratory disorder
- have a history of kidney and/or liver disease
- have recently received a gadolinium-based contrast agent
- have a history of heart rhythm disturbances, or cardiac disease
- are taking any prescription or over-the counter medications

Gadolinium-based contrast agents, including VASOVIST, increase the risk for NSF in patients with severe renal insufficiency or acute renal insufficiency of any severity due to the hepato-renal syndrome or in the perioperative setting of liver transplantation. Patients with less severe renal insufficiency who receive repetitive administrations of a gadolinium-based contrast agent may have an increased risk for the development of NSF, especially if the time interval between the administrations precludes clearance of the previously administered contrast agent from the body. If VASOVIST is administered in these situations, instruct patients to contact their physician or healthcare provider if they develop signs or symptoms of NSF, such as burning, itching, swelling, scaling, hardening and tightening of the skin, red or dark patches on the skin, stiffness in joints with trouble moving, bending or straightening of the arms, hands, legs, or feet, pain deep in the hip bones or ribs, or muscle weakness [see Warnings and Precautions (5.1)].

Inform patients that they may experience:

- reactions at the injection site, such as: redness, mild and transient burning or pain or feeling of warmth or coldness
- side effects of itching or nausea

Distributed by Bayer Healthcare, Inc., Wayne, NJ

Co-Developed by EPIX Pharmaceuticals, Inc., Lexington, MA

US Patents: 7,060,250; 7,229,606; and 5,919,967